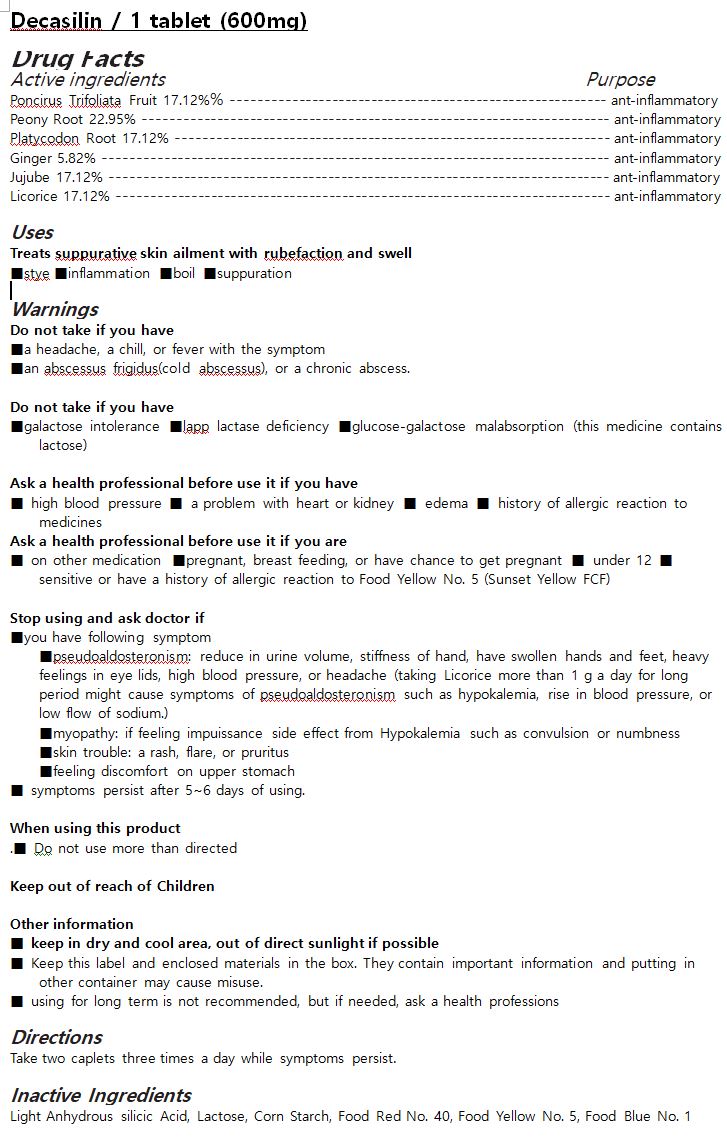 DRUG LABEL: Decasilin
NDC: 72850-0005 | Form: CAPSULE
Manufacturer: Chunwoo Pharmaceutical Co., Ltd.
Category: otc | Type: HUMAN OTC DRUG LABEL
Date: 20191112

ACTIVE INGREDIENTS: PONCIRUS TRIFOLIATA FRUIT 17.12 1/100 1; PAEONIA LACTIFLORA ROOT 22.95 1/100 1; GINGER 5.82 1/100 1; PLATYCODON GRANDIFLORUS ROOT 17.12 1/100 1; JUJUBE FRUIT 17.12 1/100 1; LICORICE 17.12 1/100 1
INACTIVE INGREDIENTS: STARCH, CORN

ACTIVE INGREDIENT

Poncirus Trifoliata Fruit 17.12%% --------------------------------------------------------- ant-inflammatory

Peony Root 22.95% ----------------------------------------------------------------------- ant-inflammatory

Platycodon Root 17.12% ------------------------------------------------------------------ ant-inflammatory

Ginger 5.82% ----------------------------------------------------------------------------- ant-inflammatory

Jujube 17.12% ---------------------------------------------------------------------------- ant-inflammatory

Licorice 17.12% --------------------------------------------------------------------------- ant-inflammatory

INACTIVE INGREDIENT

Light Anhydrous silicic Acid, Lactose, Corn Starch, Food Red No. 40, Food Yellow No. 5, Food Blue No. 1

PURPOSE

Treats suppurative skin ailment with rubefaction and swell

■stye ■inflammation ■boil ■suppuration

KEEP OUT OF REACH OF CHILDREN

WARNING

Do not take if you have

■a headache, a chill, or fever with the symptom

■an abscessus frigidus(cold abscessus), or a chronic abscess.

■galactose intolerance, lapp lactase deficiency or glucose-galactose malabsorption (this medicine contains lactose)

Ask a health professional before use it if you

■have high blood pressure

■have a problem with heart or kidney

■have edema

■are on other medication

■are pregnant, breast feeding, or have chance to get pregnant

■have a history of allergic reaction to medicines

■are under 12

■are sensitive or have a history of allergic reaction to Food Yellow No. 5 (Sunset Yellow FCF)

Stop using and ask doctor

■If you have following symptom

■pseudoaldosteronism: reduce in urine volume, stiffness of hand, have swollen hands and feet, heavy feelings in eye lids, high blood pressure, or headache (taking Licorice more than 1 g a day for long period might cause symptoms of pseudoaldosteronism such as hypokalemia, rise in blood pressure, or low flow of sodium.)

■myopathy: if feeling impuissance side effect from Hypokalemia such as convulsion or numbness

■skin trouble: a rash, flare, or pruritus

■feeling discomfort on upper stomach

■ if symptoms persist after 5~6 days of using.

When using this product

■ using for long term is not recommended, but if needed, ask a health professions.

■ Do not exceed the recommended dosage

Keep out of reach of Children

Other information

■ keep in dry and cool area, out of direct sunlight if possible

■ Keep this label and enclosed materials in the box. They contain important information and putting in other container may cause misuse.

USES

for oral use only

INDICATION & USAGE SECTION

Take two caplets three times a day while symptoms persist.